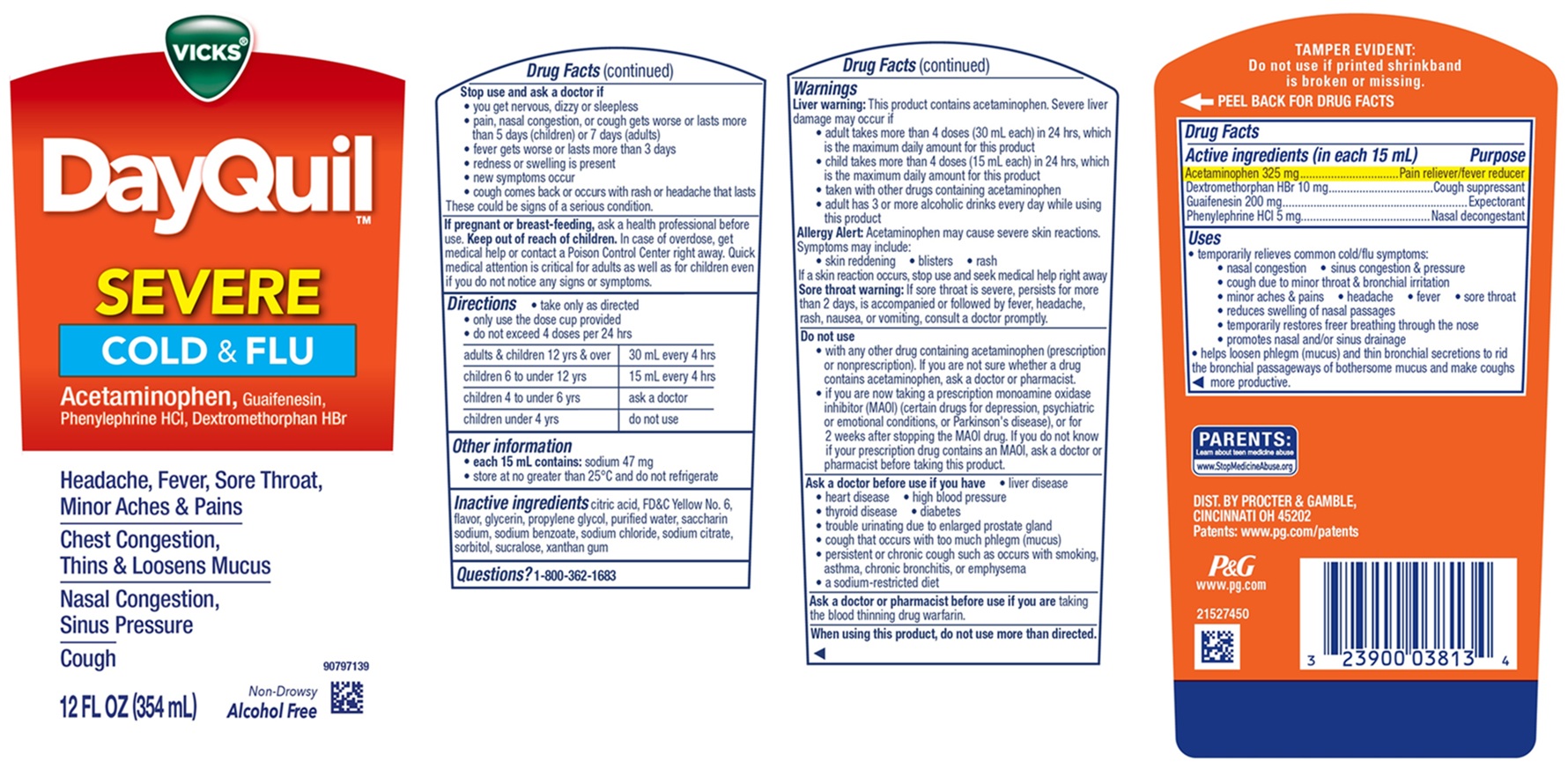 DRUG LABEL: Vicks DayQuil

NDC: 37000-810 | Form: SOLUTION
Manufacturer: The Procter & Gamble Manufacturing Company
Category: otc | Type: HUMAN OTC DRUG LABEL
Date: 20260220

ACTIVE INGREDIENTS: ACETAMINOPHEN 325 mg/15 mL; DEXTROMETHORPHAN HYDROBROMIDE 10 mg/15 mL; GUAIFENESIN 200 mg/15 mL; PHENYLEPHRINE HYDROCHLORIDE 5 mg/15 mL
INACTIVE INGREDIENTS: CITRIC ACID MONOHYDRATE; FD&C YELLOW NO. 6; GLYCERIN; PROPYLENE GLYCOL; WATER; SACCHARIN SODIUM; SODIUM BENZOATE; SODIUM CHLORIDE; SODIUM CITRATE; SORBITOL; SUCRALOSE; XANTHAN GUM

Vicks® DayQuil™ Severe Cold & Flu Liquid

Drug Facts

Active ingredients (in each 15 mL)

Acetaminophen 325 mg
Dextromethorphan HBr 10 mg
Guaifenesin 200 mg
Phenylephrine HCl 5 mg

Purpose

Pain reliever/fever reducer
Cough suppressant
Expectorant
Nasal decongestant

Uses

- temporarily relieves common cold/flu symptoms:
  - nasal congestion
  - sinus congestion & pressure
  - cough due to minor throat & bronchial irritation
  - minor aches & pains
  - headache
  - fever
  - sore throat
  - reduces swelling of nasal passages
  - temporarily restores freer breathing through the nose
  - promotes nasal and/or sinus drainage
  - helps loosen phlegm (mucus) and thin bronchial secretions to rid the bronchial passageways of bothersome mucus and make coughs more productive.

Warnings

Liver warning:This product contains acetaminophen. Severe liver damage may occur if

• adult takes more than 4 doses (30 mL each) in 24 hrs, which is the maximum daily amount for this product

• child takes more than 4 doses (15 mL each) in 24 hrs, which is the maximum daily amount for this product

• taken with other drugs containing acetaminophen

• adult has 3 or more alcoholic drinks every day while using this product

Allergy Alert:Acetaminophen may cause severe skin reactions.

Symptoms may include:

• skin reddening

• blisters

• rash

If a skin reaction occurs, stop use and seek medical help right away.

Sore throat warning: If sore throat is severe, persists for more than 2 days, is accompanied or followed by fever, headache, rash, nausea, or vomiting, consult a doctor promptly.

Do not use

• with any drug containing acetaminophen (prescription or nonprescription). If you are not sure whether a drug contains acetaminophen, ask a doctor or pharmacist.

• if you are now taking a prescription monoamine oxidase inhibitor (MAOI) (certain drugs for depression, psychiatric or emotional conditions, or Parkinson's disease), or for 2 weeks after stopping the MAOI drug. If you do not know if your prescription drug contains an MAOI, ask a doctor or pharmacist before taking this product.

Ask a doctor before use if you have

- liver disease
- heart disease
- high blood pressure
- thyroid disease
- diabetes
- trouble urinating due to enlarged prostate gland
- cough that occurs with too much phlegm (mucus)
- persistent or chronic cough such as occurs with smoking, asthma, chronic bronchitis, or emphysema
- a sodium-restricted diet

Ask a doctor or pharmacist before use if you are

taking the blood thinning drug warfarin.

When using this product,

do not use more than directed.

Stop use and ask a doctor if

- you get nervous, dizzy or sleepless
- pain, nasal congestion, or cough gets worse or lasts more than 5 days (children) or 7 days (adults)
- fever gets worse or lasts more than 3 days
- redness or swelling is present
- new symptoms occur
- cough comes back or occurs with rash or headache that lasts.
  These could be signs of a serious condition.

If pregnant or breast-feeding,

ask a health professional before use.

Keep out of reach of children.

OVERDOSAGE

In case of overdose, get medical help or contact a Poison Control Center right away. Quick medical attention is critical for adults as well as for children even if you do not notice any signs or symptoms.

Directions

- take only as directed
- only use the dose cup provided
- do not exceed 4 doses per 24 hrs

adults & children 12 yrs & over | 30 mL every 4 hrs
children 6 to under 12 yrs | 15 mL every 4 hrs
children 4 to under 6 yrs | ask a doctor
children under 4 yrs | do not use

Other information

- each 15 mL contains:sodium 47 mg
- store at no greater than 25ºC and do not refrigerate

Inactive ingredients

citric acid, FD&C Yellow No. 6, flavor, glycerin, propylene glycol, purified water, saccharin sodium, sodium benzoate, sodium chloride, sodium citrate, sorbitol, sucralose, xanthan gum

Questions?

1-800-362-1683

TAMPER EVIDENT: Do not use if printed shrinkband is broken or missing.

DIST. BY PROCTER & GAMBLE, CINCINNATI, OH 45202

PRINCIPAL DISPLAY PANEL - 354 ml Bottle Label

VICKS®

DayQuil™
SEVERE

COLD & FLU

Acetaminophen, Guaifenesin, Phenylephrine HCl, Dextromethorphan HBr

Headache, Fever, Sore Throat, Minor Aches & Pains
Chest Congestion, Thins & Loosens Mucus

Nasal Congestion, Sinus Pressure

Cough

Non-Drowsy
Alcohol Free

12 FL OZ (354 ml)